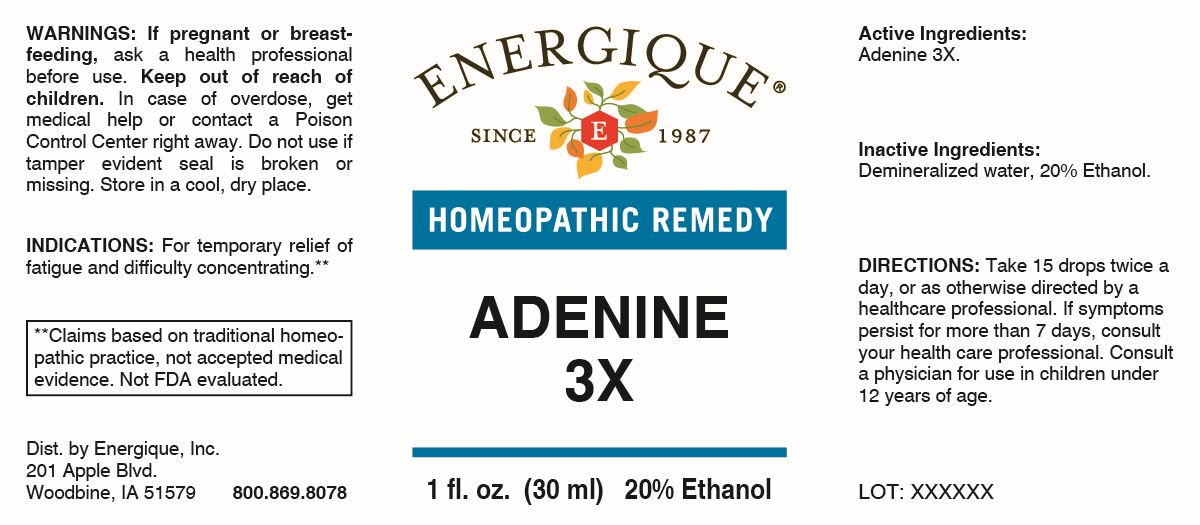 DRUG LABEL: Adenine 3X
NDC: 44911-0745 | Form: LIQUID
Manufacturer: Energique, Inc.
Category: homeopathic | Type: HUMAN OTC DRUG LABEL
Date: 20260226

ACTIVE INGREDIENTS: ADENINE 3 [hp_X]/1 mL
INACTIVE INGREDIENTS: WATER; ALCOHOL

DRUG FACTS:

ACTIVE INGREDIENTS:

Adenine 3X.

PURPOSE:

For temporary relief of fatigue and difficulty concentrating.**

** Claims based on traditional homeopathic practice, not accepted medical evidence. Not FDA evaluated.

WARNINGS:

If pregnant or breast-feeding, ask a health professional before use.

Keep out of reach of children. In case of overdose, get medical help or contact a Poison Control Center right away.

Do not use if tamper evident seal is broken or missing.

Store in a cool, dry place.

KEEP OUT OF REACH OF CHILDREN:

In case of overdose, get medical help or contact a Poison Control Center right away.

DIRECTIONS:

Take 15 drops twice a day, or as otherwise directed by a health care professional. If symptoms persist for more than 7 days, consult your health care professional. Consult a physician for use in children under 12 years of age.

USES:

For temporary relief of fatigue and difficulty concentrating.**

** Claims based on traditional homeopathic practice, not accepted medical evidence. Not FDA evaluated.

INACTIVE INGREDIENTS:

Demineralized water, 20% Ethanol.

QUESTIONS:

Dist. by Energique, Inc.

201 Apple Blvd.

Woodbine, IA 51579

800.869.8078

PACKAGE DISPLAY LABEL:

ENERGIQUE

SINCE 1987

HOMEOPATHIC REMEDY

ADENINE 3X

1 fl. oz. (30 ml)